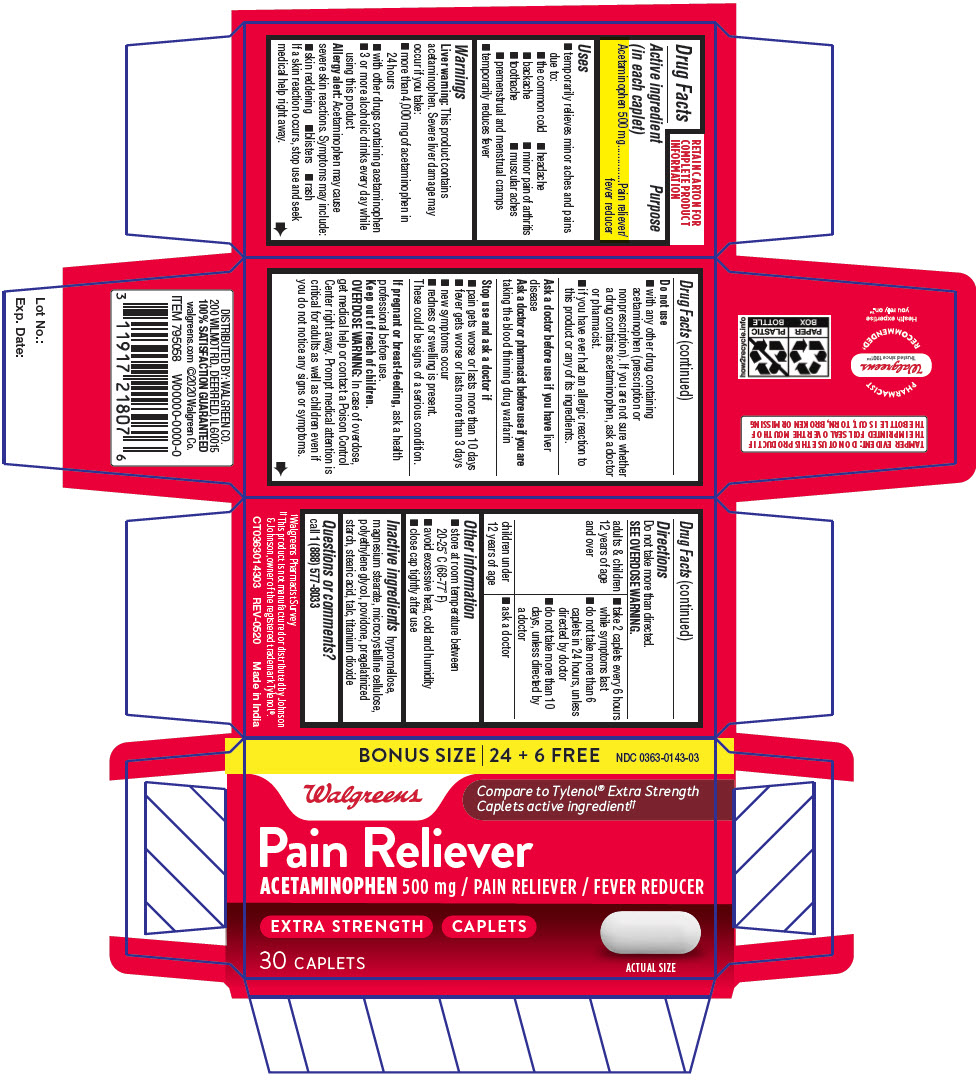 DRUG LABEL: ACETAMINOPHEN
NDC: 0363-0143 | Form: TABLET, FILM COATED
Manufacturer: Walgreens Co.
Category: otc | Type: HUMAN OTC DRUG LABEL
Date: 20220506

ACTIVE INGREDIENTS: ACETAMINOPHEN 500 mg/1 1
INACTIVE INGREDIENTS: hypromellose, unspecified; magnesium stearate; microcrystalline cellulose; polyethylene glycol, unspecified; povidone, unspecified; stearic acid; talc; titanium dioxide

ACETAMINOPHEN

Drug Facts

Active ingredient (in each caplet)

Acetaminophen 500 mg

Purpose

Pain reliever/fever reducer

Uses

- temporarily relieves minor aches and pains due to:
  - the common cold
  - headache
  - backache
  - minor pain of arthritis
  - toothache
  - muscular aches
  - premenstrual and menstrual cramps
- temporarily reduces fever

Warnings

Liver warning

This product contains acetaminophen. Severe liver damage may occur if you take:

- more than 4,000 mg of acetaminophen in 24 hours
- with other drugs containing acetaminophen
- 3 or more alcoholic drinks every day while using this product

Allergy alert

Acetaminophen may cause severe skin reactions. Symptoms may include:

- skin reddening
- blisters
- rash

If a skin reaction occurs, stop use and seek medical help right away.

Do not use

- with any other drug containing acetaminophen (prescription or nonprescription). If you are not sure whether a drug contains acetaminophen, ask a doctor or pharmacist.
- if you have ever had an allergic reaction to this product or any of its ingredients.

Ask a doctor before use if you have liver disease

Ask a doctor or pharmacist before use if you are taking the blood thinning drug warfarin

Stop use and ask a doctor if

- pain gets worse or lasts more than 10 days
- fever gets worse or lasts more than 3 days
- new symptoms occur
- redness or swelling is present.

These could be signs of a serious condition.

PREGNANCY OR BREAST FEEDING

If pregnant or breast-feeding, ask a health professional before use.

Keep out of reach of children.

OVERDOSE WARNING

In case of overdose, get medical help or contact a Poison Control Center right away. Prompt medical attention is critical for adults as well as children even if you do not notice any signs or symptoms.

Directions

Do not take more than directed.

SEE OVERDOSE WARNING.

adults & children 12 years of age and over | - take 2 caplets every 6 hours while symptoms last - do not take more than 6 caplets in 24 hours, unless directed by doctor - do not take more than 10 days, unless directed by a doctor
children under 12 years of age | - ask a doctor

Other information

- store at room temperature between 20-25° C (68-77° F)
- avoid excessive heat, cold and humidity
- close cap tightly after use

Inactive ingredients

hypromellose, magnesium stearate, microcrystalline cellulose, polyethylene glycol, povidone, pregelatinized starch, stearic acid, talc, titanium dioxide

Questions or comments?

call 1 (888) 577-8033

DISTRIBUTED BY: WALGREEN CO.
200 WILMOT RD., DEERFIELD, IL 60015

PRINCIPAL DISPLAY PANEL - 30 Caplet Bottle Carton

BONUS SIZE | 24 + 6 FREE
NDC 0363-0143-03

Walgreens

Compare to Tylenol® Extra Strength
Caplets active ingredient††

Pain Reliever
ACETAMINOPHEN 500 mg / PAIN RELIEVER / FEVER REDUCER

EXTRA STRENGTH
CAPLETS

30 CAPLETS

ACTUAL SIZE